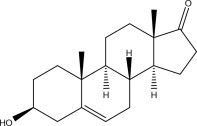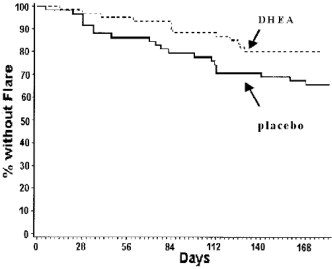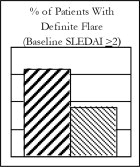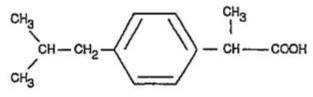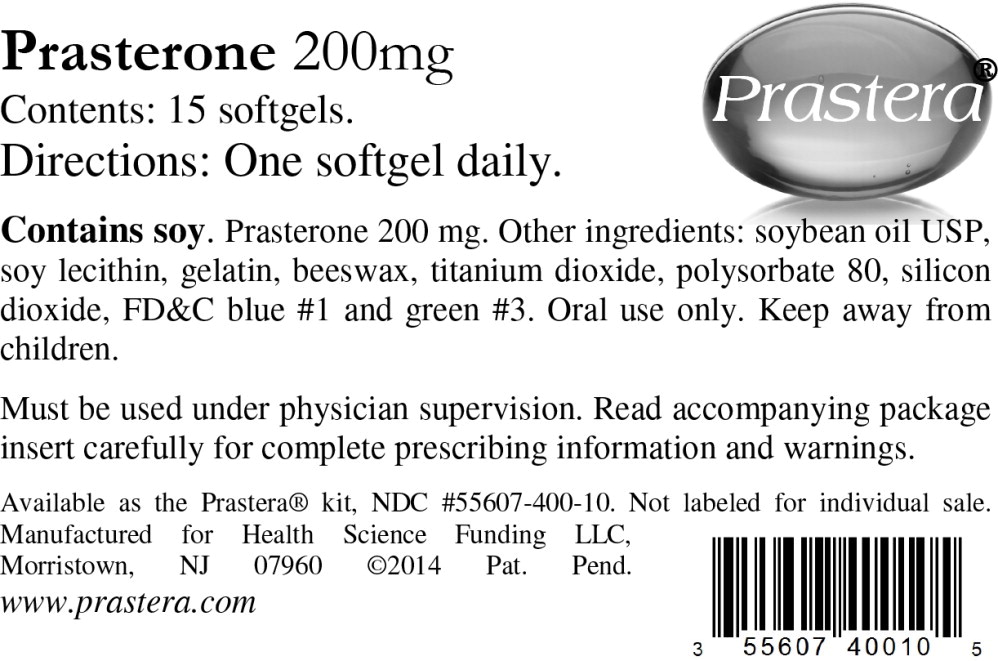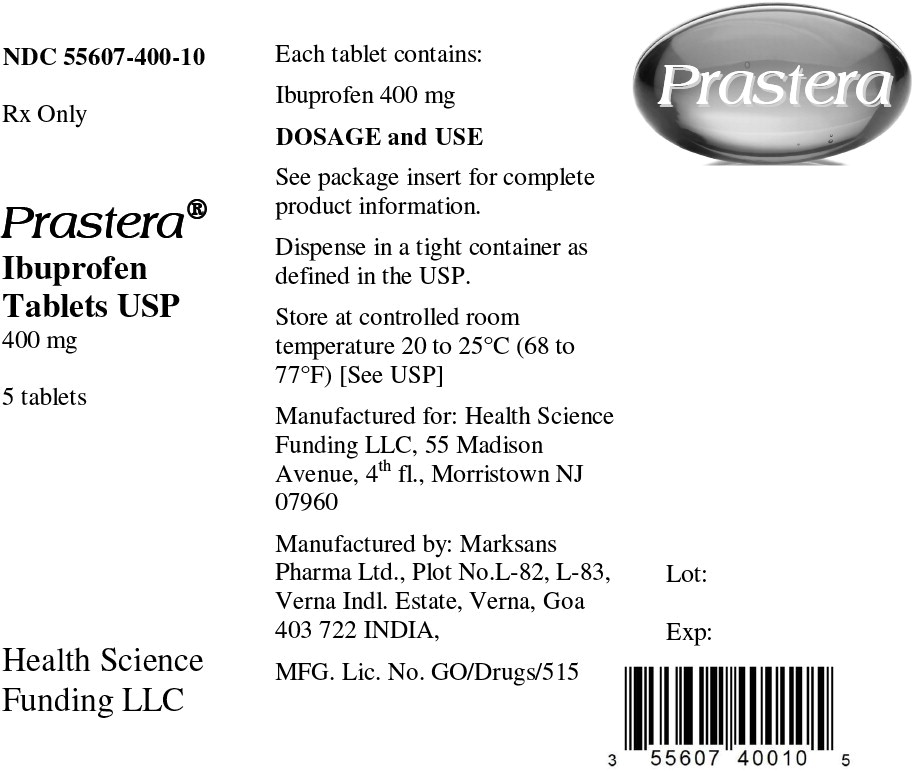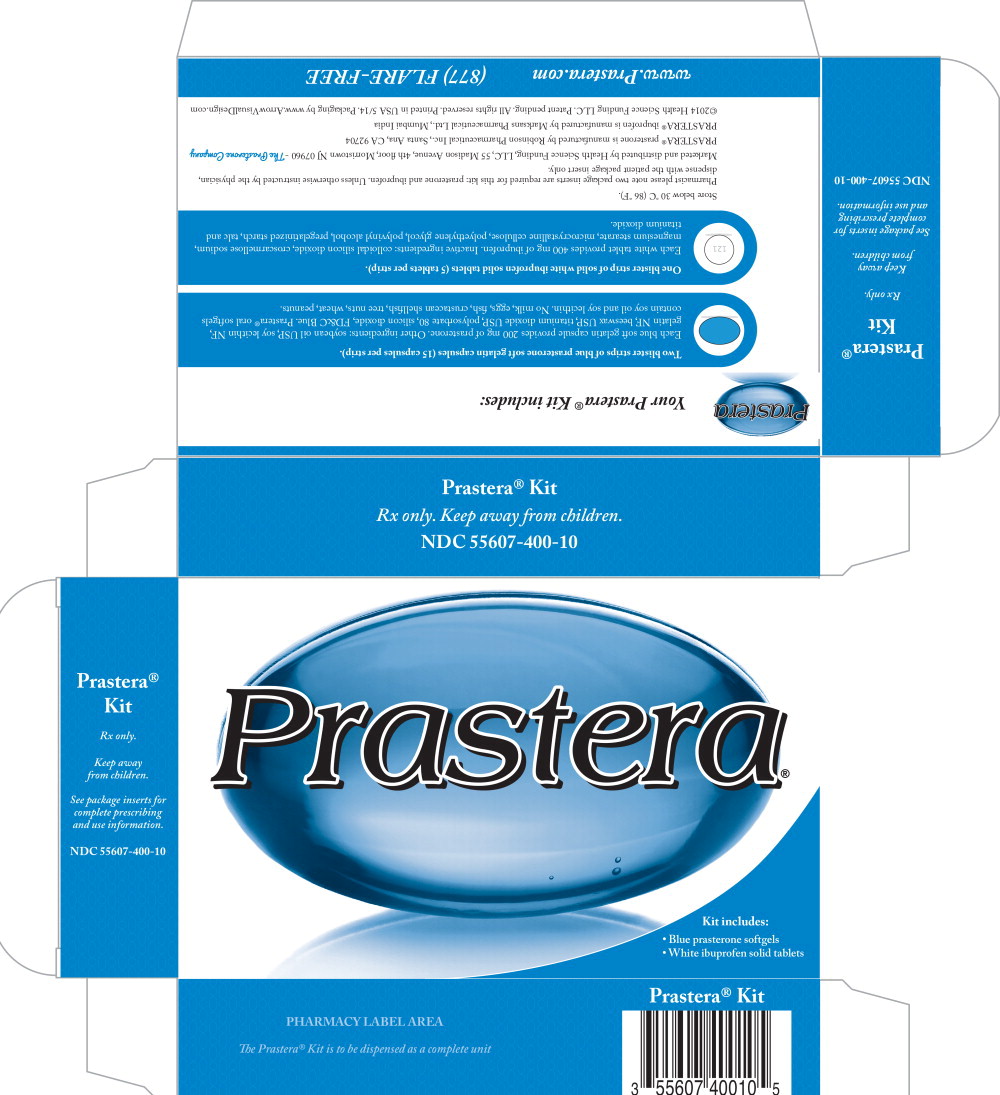 DRUG LABEL: Prastera
NDC: 55607-400 | Form: KIT | Route: ORAL
Manufacturer: Health Science Funding, LLC
Category: prescription | Type: HUMAN PRESCRIPTION DRUG LABEL
Date: 20140225

ACTIVE INGREDIENTS: Prasterone 200 mg/1 1; ibuprofen 400 mg/1 1
INACTIVE INGREDIENTS: soybean oil; lecithin, soybean; gelatin; yellow wax; titanium dioxide; polysorbate 80; silicon dioxide; FD&C Blue No. 1; COLLOIDAL SILICON DIOXIDE; CROSCARMELLOSE SODIUM; MAGNESIUM STEARATE; CELLULOSE, MICROCRYSTALLINE; POLYETHYLENE GLYCOLS; POLYVINYL ALCOHOL; STARCH, CORN; TALC; TITANIUM DIOXIDE

HIGHLIGHTS OF PRESCRIBING INFORMATION

These highlights do not include all the information needed to use PRASTERA® safely and effectively. See full prescribing information for PRASTERA®.
PRASTERA® prasterone oral softgels 200mg are for oral use only.
Initial U.S. Approval

1 INDICATIONS AND USAGE

PRASTERA® prasterone 200 mg oral softgels is indicated in female patients with mild to moderate, active (SLEDAI ≥2) systemic lupus erythematosus (SLE) to restore serum 5-dehydroandrosterone sulfate to levels typical of women without SLE. In Phase III clinical trials in female patients with mild to moderate active SLE, prasterone 200 mg was associated with reduced risk of auto-immune flare, reduced risk of breast cancer and reduced risk of death from any cause. (§§1, 6.2, 6.4, 6.5)

2 DOSAGE AND ADMINISTRATION

The recommended dose is one (1) softgel daily. (§2)

3 DOSAGE FORMS AND STRENGTHS

200mg oral softgel capsules supplied in a convenience package with ibuprofen oral tablets 400mg. (§3)

4 CONTRAINDICATIONS

- Known hypersensitivity to any of its ingredients. (§4)
- Undiagnosed abnormal genital bleeding. (§4)
- Known, suspected or history of breast cancer. (§4, §6.5)
- History of, or known, deep vein thrombosis, pulmonary embolism, arterial thromboembolic disease (e.g., stroke, myocardial infarction). (§4)
- Hypercholesterolemia or ischemic heart disease. (§4, §7.2.4)
- Hepatic or renal impairment (pharmacokinetic data lacking). (§4, §7.2)
- Breast-feeding or known or suspected pregnancy. (§4)
- History of psychiatric disorder. (§4, §8)

5 WARNINGS AND PRECAUTIONS

- PRASTERA® is not intended for use in nursing or pregnant women, children nor males (safety data is lacking). (§§4, 9)
- PRASTERA® use may be prohibited by certain athletic anti-doping regulations. (§9.5)
- PRASTERA® may in certain patients elevate serum levels of 5-dehydroepiandrosterone, testosterone or estrogen above the normal range for healthy, non-afflicted women of similar age. Periodic measurement of serum hormones is prudent. (§7.2.1)
- Hypertension may occur with prasterone treatment. Monitor blood pressure closely. (§6.3.2)

6 ADVERSE REACTIONS

The most common adverse event with PRASTERA® is acne. This is generally treatable with topical anti-acne medication. (§6.1)

Another common adverse reaction is hirsutism. Both acne and hirsutism are reversible on cessation of prasterone. (§6.1)

To report SUSPECTED ADVERSE REACTIONS, contact 1 (855) FLARE-FREE or FDA (1-800-FDA-1088 or www.fda.gov/medwatch) or your doctor.

8 DRUG INTERACTIONS

- PRASTERA® may interact with certain psychiatric drugs. (§8)
- Concomitant administration of PRASTERA® with endogenous testosterone or estrogens, or dietary supplements containing DHEA or dehydroepiandrosterone, is not generally recommended unless serum sex hormone levels are monitored, because of the potential to elevate levels above the ranges considered normal in healthy individuals. (§§7.1, 7.2.1, 8, 10, 16.3)

9 USE IN SPECIFIC POPULATIONS

- Not recommended for use in nursing nor pregnant women, pediatric patients, or men (safety data is lacking). (§9)

FULL PRESCRIBING INFORMATION

1 INDICATIONS AND USAGE

Oral prasterone (200mg per day) in female patients with active systemic lupus erythematosus (SLE) has in several blinded, placebo-controlled randomized clinical studies been associated with a reduced risk of auto-immune flare, §§6.2, 14.1.1, a reduced risk of breast cancer and a reduced risk of death from any cause, §§6.4, 14.2.

Patients with SLE may have depressed serum levels of 5-dehydroepiandrosterone sulfate (5-DHEAS). Oral prasterone has been shown to restore SLE patients' serum 5-DHEAS levels. Prastera® oral softgels are intended for use in patients for whom medical evaluation shows a depressed serum level of DHEA and thus a distinctive need for exogenous DHEA. Prastera® oral prasterone softgels are intended to be used under medical supervision, for a patient receiving active and ongoing medical supervision, wherein the patient obtains medical care on a recurring basis for, among other things, instructions on the use of this product. Prastera® oral prasterone softgels are intended for the dietary management of SLE by meeting the distinctive nutritional requirement of women with mild-to-moderate active SLE. Prastera® oral prasterone softgels are intended for oral intake only.

Prastera® does not cure, treat, mitigate or prevent SLE. To the contrary, patients taking Prastera® will continue to have SLE, and thus may continue to require other appropriate therapy.

2 DOSAGE AND ADMINISTRATION

2.1 General Instructions

The recommended dose is one 200mg oral softgel daily, with or without food.

2.2 Special Precautions

None.

3 DOSAGE FORMS AND STRENGTHS

Prastera® oral prasterone is provided as oral softgels. Each softgel contains 200mg of prasterone (≥99% pure). Other ingredients: soybean oil USP, soy lecithin NF, gelatin NF, beeswax USP, titanium dioxide USP, polysorbate 80, silicon dioxide, FD&C Blue.

4 CONTRAINDICATIONS

Prastera® oral softgels should not be used in patients with any of the following conditions:

1. Known hypersensitivity to prasterone, DHEA, testosterone, estrogens or any component of Prastera® oral prasterone softgels. §4.1.
2. Undiagnosed abnormal genital bleeding.
3. Known, suspected, or history of breast cancer. §6.5.
4. Active deep vein thrombosis, pulmonary embolism or history of these conditions.
5. Active arterial thromboembolic disease (for example, stroke and myocardial infarction), or a history of these conditions. §6.3.2.
6. Hypercholesterolemia, §7.2.4, or ischemic heart disease.
7. Liver disease or renal impairment (pharmacokinetic data lacking).
8. Known or suspected pregnancy; breast-feeding (safety data lacking).
9. History of psychiatric disorders (risk of exacerbation). The risk of mania may be increased during concomitant use with antidepressants (tricyclic or SSRIs) and/or alcohol, or with high prasterone doses, or in patients with a history of mood disorders.

4.1 Allergy Warning

Prastera® oral softgels contain soy oil and soy lecithin. No milk, eggs, fish, crustacean shellfish, tree nuts, wheat, peanuts.

5 WARNINGS AND PRECAUTIONS

PRASTERA® is not intended for use in children, nor males, nor women who are breastfeeding, pregnant, or who expect to become pregnant. §9. Monitoring of blood pressure, serum lipids, serum sex hormones is prudent. See Clinical Laboratory Evaluation, §§7.2.1, 7.2.4.

6 ADVERSE REACTIONS

The most-frequent adverse reactions observed in placebo-controlled, blinded clinical studies GL94-01, GL95-01, GL95-02 and GLB96-01 are as follows:

6.1 Increased Risk of Acne and Hirsutism

Acne was the most frequently reported adverse event. Acne was reported less frequently by African American patients, in approximately 26%, compared to approximately 36% in Caucasian patients.

The second most-frequent adverse event was hirsutism. In study GLB96-01 involving patients of Chinese extraction, hirsutism was not reported; this may indicate a decreased racial susceptibility to hirsutism.

Acne and hirsutism were both reversible on cessation of prasterone therapy. In addition, both were more likely to be reported early in treatment; patients who had not developed these within the first 6 months of exposure are less likely to develop them later.

6.2 Reduced Risk of Myalgia and Other Flare Symptoms

Placebo-treated patients had higher incidences of myalgia, joint disorder, anorexia, nasal ulcers and LE skin rash than did prasterone-treated patients. These differences may be due to the decreased risk of flare observed in prasterone-treated patients. §14.1.

6.3 Other Common Adverse Events

No adverse events increase in frequency with longer duration of treatment. The Table displays all adverse events reported in a frequency of 10% or greater from either the 200 mg dose group or the placebo group for the pooled double-blind phases of Studies GL94-01 and GL95-02. Because the number of patients who received prasterone 100 mg was substantially fewer, adverse events for this group are only presented for those adverse events which were reported in ≥ 10% of either placebo or prasterone 200 mg patients.

ADVERSE EVENTS WITH FREQUENCY ≥10%* (pooled GL94-01 and GL95-02 results)
COSTART TERM | Placebo N=256 | 200mg N=253
Rash | 77 (30.1%) | 93 (36.8%)
Acne | 39 (15.2%) | 91 (36.0%) **
Arthralgia | 95 (37.1%) | 88 (34.8%)
Asthenia | 70 (27.3%) | 68 (26.9%)
Headache | 76 (29.7%) | 60 (23.7%)
Arthritis | 58 (22.7%) | 57 (22.5%)
Myalgia | 79 (30.9%) | 55 (21.7%) **
Pain Abdomen | 34 (13.3%) | 41 (16.2%)
Flu Syndrome | 46 (18.0%) | 40 (15.8%)
Stomatitis Ulcer | 50 (19.5%) | 38 (15.0%)
Hirsutism | 6 (2.3%) | 36 (14.2%) **
Fever | 39 (15.2%) | 36 (14.2%)
Depression | 33 (12.9%) | 35 (13.8%)
Alopecia | 48 (18.8%) | 35 (13.8%)
Infection | 37 (14.5%) | 26 (10.3%)
Sinusitis | 33 (12.9%) | 22 (8.7%)
Pain Chest | 27 (10.5%) | 22 (8.7%)
*Frequency > 10% in either prasterone 200 mg or placebo patients.
** P< 0.05, Placebo vs. prasterone 200 mg.

For adverse events occurring in < 10% of patients, the following showed an absolute difference of at least 3% between placebo or prasterone 200 mg, or, if less than 3% difference, the difference was significant (p < 0.05):

ADVERSE EVENTS WITH FREQUENCY <10% AND AT LEAST A 3% OR A SIGNIFICANT DIFFERENCE (pooled GL94-01 and GL95-02 results)
COSTART TERM | Placebo N=256 | prasterone 200 mg N=253
Less Frequent in Prasterone
Anorexia | 10 (3.9%) | 2 (0.8%) **
Nasal Septum Disorder (nasal ulcers) | 14 (5.5%) | 5 (2.0%) **
Rash Lupus Erythematosus | 13 (5.1%) | 4 (1.6%) **
Joint Disorder | 14 (5.5%) | 4 (1.6%) **
More Frequent in Prasterone
Creatinine Increase | 0 (0.0%) | 6 (2.4%)**
Hypertension | 7 (2.7%) | 20 (7.9%) **
Hematuria | 1 (0.4%) | 9 (3.6%) **
Insignificant Difference
Back Pain | 16 (6.3%) | 24 (9.5%)
Pharyngitis | 14 (5.5%) | 6 (2.4%)
Dyspnea | 22 (8.6%) | 11 (4.3%)
Lymphadenopathy | 21 (8.2%) | 12 (4.7%)
** P< 0.05, Placebo vs. prasterone 200 mg.

The pattern of adverse events in clinical study GLB96-01 showed a similar, but not identical pattern. Acne was the most common adverse event; this may reflect the fact that almost all patients were also receiving corticosteroids. This may also reflect racial differences in sensitivity to prasterone. By contrast, hirsutism was not reported at all in GLB96-01.

ADVERSE EVENTS REPORTED BY AT LEAST 10% OF EITHER TREATMENT GROUP (GBL96-01)
 | Placebo N= 59 | Treatment N= 61
Arthralgia | 37 (62.7%) | 39 (63.9%)
Acne * | 17 (28.8%) | 36 (59.0%)*
Pharyngitis | 32 (54.2%) | 34 (55.7%)
Myalgia | 24 (40.7%) | 28 (45.9%)
Headache * | 37 (62.7%) | 26 (42.6%)*
Pain Abdomen | 25 (42.4%) | 23 (37.7%)
Asthenia | 19 (32.2%) | 18 (29.5%)
Cough Increase | 18 (30.5%) | 18 (29.5%)
Dizziness | 19 (32.2%) | 15 (24.6%)
Pain Chest | 11 (18.6%) | 14 (23.0%)
Dyspnea | 8 (13.6%) | 14 (23.0%)
Rash | 16 (27.1%) | 14 (23.0%)
Fever | 17 (28.8%) | 13 (21.3%)
Alopecia | 8 (13.6%) | 13 (21.3%)
Pain | 8 (13.6%) | 11 (18.0%)
Diarrhea | 11 (18.6%) | 11 (18.0%)
Rhinitis | 13 (22.0%) | 11 (18.0%)
Stomatitis Ulcer | 17 (28.8%) | 10 (16.4%)
Pain Back | 10 (16.9%) | 9 (14.8%)
Edema | 6 (10.2%) | 9 (14.8%)
Injury Accident | 6 (10.2%) | 8 (13.1%)
Insomnia | 7 (11.9%) | 8 (13.1%)
Pruritus | 7 (11.9%) | 8 (13.1%)
Infection* | 15 (25.4%) | 6 (9.8%)*
Dry Eye | 10 (16.9%) | 6 (9.8%)
Vomit | 8 (13.6%) | 5 (8.2%)
Peripheral Edema | 8 (13.6%) | 5 (8.2%)
Rash Lupus Erythematosus | 7 (11.9%) | 5 (8.2%)
Conjunctivitis | 7 (11.9%) | 5 (8.2%)
Nausea | 9 (15.3%) | 4 (6.6%)
*P-value<0.05, Treatment vs. Placebo, chi-square test

Of adverse events reported by at least 10% of patients, acne was the only event significantly more frequent in the treatment group. Headache and infection were more frequent in the placebo group. Of the adverse events reported with an incidence of less than 10%, the only statistically significant difference was for seborrhea (0 placebo vs. 5 treatment patients).

6.3.1 Hypertension

Hypertension was reported as an adverse event more frequently in the prasterone 200 mg group than placebo. When measures of increased (changed) blood pressure were included, there appeared to be no difference between the groups. Whether prasterone increases hypertension is thus not clear.

6.4 Reduced Risk of Death

In the GL94-01, GL95-01 and GL95-02 placebo-controlled clinical studies (pooled data), the placebo group experienced 6 deaths in 77 patients, a risk of death of 7.8%. In contrast, the prasterone group (pooled treatment and cross-over) experienced 8 deaths in 495 patients, a risk of death of 1.6%. The risk of death from any cause was therefore five times higher in the placebo group.

6.5 Reduced Risk of Breast Cancer

In the GL94-01, GL95-01 and GL95-02 placebo-controlled clinical studies (pooled data), incidence of breast cancer was 1 in 336 patient-years (0.29%) for placebo and 3 in 1573 patient-years (0.19%) for prasterone (pooled treatment and cross-over). Prasterone was thus associated with reducing the risk of breast cancer by one third.

For patients over 44 years of age, the difference between placebo and prasterone groups was more pronounced. For women at least 45 years of age, the rate of breast cancer was 1 in 24 patient-years (4.2%) for placebo and 3 in 206 patient-years (1.5%) for prasterone treatment and cross-over patients. Prasterone was thus associated with reducing the risk of breast cancer by two thirds.

6.6 Other Serious Adverse Events

Adverse events that were assessed as “severe” occurred in similar frequencies in both treatment and placebo groups, with asthenia being the most common adverse event reported as severe in both placebo and treated patients. Although the patient numbers are small, abdominal pain reported as a severe adverse event occurred in 6 treated 200 mg patients, 2 treated 100mg patients, and no placebo patients.

Serious adverse events occurred in 39 200 mg, 7 100 mg, and 47 placebo patients participating in GL94-01 and GL95-02. However, only 3 serious adverse events were considered possibly related, 2 in the placebo group (one suicide and one patient with menomettrorhagia) and one in 200 mg (a patient with an acute psychosis).

In the Taiwan study, serious adverse events were reported in a significantly higher proportion of patients in the placebo group than in the treatment group. In most cases, the types of serious adverse events reported were consistent with SLE flares or hospitalization for manifestations of SLE, rather than adverse effects of the study drug.

SEVERE ADVERSE EVENTS OCCURRING IN AT LEAST 2 PATIENTS* (GL94-01 and GL95-02)
COSTART TERM | Placebo N=256 | prasterone 200 mg N=253
Asthenia | 22 (8.6%) | 22 (8.7%)
Headache | 11 (4.3%) | 8(3.2%)
Arthralgia | 6 (2.3%) | 6 (2.4%)
Pain Abdomen | 0 (0%) | 6 (2.4%)
Rash | 5 (2.0%) | 6 (2.4%)
Arthritis | 2 (0.8%) | 5 (2.0%)
Dyspnea | 1 (0.4%) | 4 (1.6%)
Depression | 4 (1.6%) | 2 (0.8%)
Diabetes Mellitus | 0 (0%) | 2 (0.8%)
Emotional Lability | 0 (0%) | 2 (0.8%)
Infection | 0 (0%) | 2 (0.8%)
Myalgia | 5 (2.0%) | 2 (0.8%)
Pain | 1 (0.4%) | 2 (0.8%)
Pain Chest | 4 (1.6%) | 2 (0.8%)
Paresthesia | 1 (0.4%) | 2 (0.8%)
Pleural Disorder | 1 (0.4%) | 2 (0.8%)
Vasculitis | 0 (0%) | 2 (0.8%)
Joint Disorder | 2 (0.8%) | 1 (0.4%)
Peripheral Edema | 2 (0.8%) | 0 (0%)
Sepsis | 2 (0.8%) | 0 (0%)
Cyst | 2 (0.8%) | 0 (0%)
Thinking Abnormal | 2 (0.8%) | 0 (0%)
*Frequency at least 2 patients in either prasterone 200 mg or placebo

7 SAFETY

7.1 Relationship Of Dose To Safety

Neither adverse events nor laboratory values showed a dose relationship.

7.2 Clinical Laboratory Evaluation

In the placebo-controlled trials, testosterone was increased in a dose related manner in SLE patients receiving prasterone.

Prasterone caused an increased number of patients (in comparison to placebo) to have a decrease in serum complement (C3). The decrease in C3 was not associated with renal dysfunction. The medical literature suggests that a decline in serum complement may be a direct effect of suppression of complement production by androgens.

The clinical studies suggest that administration of prasterone causes an early, but not progressive, decrease in serum lipids, primarily HDL-C and triglycerides. It would be prudent to follow NCEP guidelines while monitoring lipids in patients receiving prasterone.

There were no changes of potential significance in liver function tests (ALT, AST, alkaline phosphatase, or total bilirubin) within and between the treatment groups. Equally, serum calcium, phosphorus, uric acid, total protein and albumin showed no clinically relevant differences.

Mean 24-hour urine protein excretion was slightly higher in the prasterone group viz placebo.

There does not appear to be a difference between placebo and prasterone for new hematuria accompanied by SLE renal involvement, as manifested by changes in urinary protein excretion, increased creatinine, or new therapy for renal SLE.

7.3 Post-Marketing Experience

The following adverse reactions have been reported with unregulated dietary supplements containing DHEA. The identity, purity and strength of the product used was not always known. It is therefore not possible to establish a causal relation to prasterone exposure.

Cardiovascular Effects: Benign premature atrial contractions and occasional premature ventricular contractions occurred in a 55-year-old man after administration of DHEA; DHEA was discontinued and arrhythmias controlled by beta-blockers. (Sahelian 1998)

One case of hepatitis has been reported in a patient with high pre-treatment anti-nuclear antibody (ANA) titers; causality is uncertain. (Buster 1992)

Manic reactions during DHEA use have been described. (Dean 2000; Pies 2000) Risk factors for development of mania / psychosis are considered to be higher doses, combined use with antidepressants, alcohol or benzodiazepines, young patients (20-30 years, with peak endogenous DHEA levels), and cytochrome P450 polymorphisms (poor metabolizers).

8 DRUG INTERACTIONS

There is no known pharmacokinetic effect (bioavailability, pharmacokinetics, or pharmacodynamics) of prasterone on prednisone or hydroxychloroquine, with the possible exception of increasing the magnitude of a decrease in triglycerides seen with hydroxyquinoline.

Prasterone may theoretically interact with one or more of the following drugs: carbamazepine, phenothiazines (e.g., acetophenazine, chlorpromazine, chlorprothixene, ethopropazine, fluphenazine, mesordiazine, methdilazine, perazine, perphenazine, pipotiazine, prochlorperazine, promazine, promethazine, propiomazine, thioridazine, trifluoperazine, triflupromazine), citalopram; escitalopram; clozapine, conjugated estrogens; estherified estrogens; estradiol; estradiol cypionate; estropipate; ethinyl estradiol, fluoxetine, fluvoxamine; haloperidol, lithium, loxapine, molindone, olanzapine, paroxetine, quetiapine, risperodone, sertraline, testosterone, triazolam and valproic acid. For further information on potential interactions with these drugs, please see The Cochrane Review monograph for prasterone.

9 USE IN SPECIFIC POPULATIONS

9.1 Males

The placebo-controlled, double-blind clinical studies involved women. Use in men at this time is not recommended because data is lacking.

9.2 Patients with Active SLE Disease

The GL94-01 and GL95-02 clinical studies showed a difference in responder rates between placebo and prasterone increased with increasing baseline SLEDAI.

9.3 Pregnancy

Safety and effectiveness in nursing and pregnant women has not been established. Use is not recommended.

9.4 Pediatric Use

Safety and effectiveness in pediatric patients have not been established. Use in pediatric patients is not recommended.

9.5 Athletic Anti-Doping

Prasterone use is prohibited by certain athletic anti-doping regulations.

10 OVERDOSE

Oral prasterone of up to 1.6 grams per day has not provoked overdose in post-menopausal women. (Mortola 2000) In case of suspected overdose, Prastera® softgels should be discontinued and the patient should be treated symptomatically.

11 DESCRIPTION

Prastera® prasterone oral softgels are oblong blue soft gelatin capsules. Each PRASTERA® prasterone oral softgel contains 200mg prasterone (>98% pure), in a lipophilic vehicle.

Prasterone is chemically identical to the naturally-occurring pro-hormone 5-dehydroepiandrosterone, secreted by the adrenal cortex, gonads and brain tissue. It is designated chemically as (3S,8R,9S,10R,13S,14S)-3-hydroxy-10,13-dimethyl-3,4,7,8,9,10,11,12,13,14,15,16 –dodecahydro-1H-cyclopenta[a]phenanthren-17(2H)-one. Its molecular weight is 288.424 g/mol. Its molecular formula is C19H28O2.

12 CLINICAL PHARMACOLOGY

Prastera® softgels are an oral dosage form of pharmaceutical-grade prasterone, chemically identical to prasterone of native human origin, in a lipophilic vehicle.

12.1 Pharmacodynamics

Oral prasterone has been shown to increase serum levels of 5-DHEAS. The precise mechanism by which normal serum levels of 5-DHEAS may act to reduce the risk of auto-immune flare, breast cancer and death is not known.

12.2 Pharmacokinetics

12.2.1 Time To Peak Concentration

Oral prasterone reaches a peak serum concentration at 1.5 to 2 hours after administration. In healthy young women (mean age, 30 years) receiving prasterone 200 mg daily (given with prednisone), mean peak plasma levels on day 29 of prasterone and 5-DHEAS were 1.3 mcg/dL (13 ng/mL) and 942 mcg/dL (9.4 mcg/mL), and occurred in 2 hours and 2.4 hours, respectively, after administration. In elderly women (mean, 69 years) and elderly men (mean, 69 years), mean peak plasma concentrations (times to peak levels) after a single 200-mg micronized oral dose were 27 ng/mL (1.4 hours) and 22 ng/mL (1.3 hours), respectively. After a single 200 mg dose, mean serum levels of 5-DHEAS increased 5-fold in men (to 7 mcg/mL) and 21-fold in women (to 7.5 mcg/mL) relative to baseline healthy levels.

12.2.2 Absorption

During two weeks of daily administration (200 mg), plasma levels (and times to peak levels) of both 5-dehydroepiandrosterone and its sulfated metabolite did not change significantly in either women or men, indicating a lack of accumulation.

12.2.3 Distribution

Approximately 10% to 20% of prasterone is bound to serum protein; approximately 80% to 90% of 5-DHEAS is bound to protein. 5-DHEAS penetrates the blood-brain barrier; cerebro-spinal fluid levels of 5-DHEAS range from 0.2% to 5% of corresponding plasma levels.

12.2.4 Metabolism

Oral prasterone is sulfated to 5-DHEAS ester in the intestine and liver by sulfotransferases. Prasterone and 5-DHEAS are converted in peripheral tissues to androstenedione, androsterone sulfate, estradiol, estriol and estrone, dihydrotestosterone, 7-oxo-prasterone, and testosterone.

12.2.5 Excretion

Prasterone (200mg dose) elimination half-life: young women, 11 hours; elderly men, 7 hours. In elderly women, the elimination half-life progressively declined, from about 12 hours (day 1), to 9 hours (day 8), to 7 hours (day 15). 5-DHEAS half-life: young women, 12 hours; elderly men, 20-25 hours; elderly women, 24-27 hours.

12.2.6 Special Populations

The pharmacokinetics of oral prasterone has not been assessed in low body weight or obese patients. There is insufficient information available from placebo-controlled clinical trials to compare prasterone pharmacokinetics in different racial groups, nor for patients with renal or hepatic impairment.

13 PRE-CLINICAL TOXICOLOGY

The non-clinical literature indicates that prasterone may be either chemo-protective or carcinogenic, depending on the model. Prasterone may thus be inhibitory or stimulatory to hormone-senentive tumors. The literature, however, suggests that prasterone is less potent than its androgenic and estrogenic metabolites. Similarly to androgenic and extrogenic compounds, it is expected to be difficult to define the carcinogenic potential of prasterone.

14 CLINICAL STUDIES

The placebo-controlled studies (GL94-01, GL95-01, GL95-02 and GLB96-01) had very different study designs and efficacy endpoints. Pooling of efficacy data is thus not meaningful. Consequently, results are presented by individual study.

14.1 Reduction In Risk Of Flare

14.1.1 Clinical Study GLB96-01

GLB96-01 was a six month, multi-center, randomized, parallel group, double-blind, placebo-controlled study of prasterone (200mg daily) in Asian women (mean age = 32 years); 97% had baseline SLEDAI score >2. The treatment group (n = 60) had a somewhat higher baseline SLEDAI than did the placebo group (n = 59).

The treatment group significantly had fewer patients with at least one definite flare. The number of patients with definite flares in the treatment group was 46.0% less than in the placebo group (18.3% vs. 33.9%, p = 0.044 based on survival analysis using Cox model).

14.1.2 Clinical Study GL95-02

Study GL95-02 was a 12 month, multi-center, randomized, parallel group, double-blind, placebo-controlled study of prasterone (200mg daily) in women (n = 346) with active SLE (SLAM score ≥7 excluding ESR, SLEDAI score >2) receiving ≤10 mg/day prednisone (or its equivalent of other cortico-steroids). A secondary efficacy variable (flare) was defined as a modified SELENA definition flare.

Three hundred eighty one (381) patients were randomized, of whom 346 were in the per-protocol population. For all patients, 47/176 (27%) of placebo and 37/170 (22%) of prasterone patients experienced a definite flare.

For the subset of patients with a baseline SLEDAI>2, treated patients had a 23.7% decrease in the risk of experiencing at least one definite flare, compared to placebo. During the study period, 41/133 (31%) of placebo patients and 31/132 (23.5%) of prasterone patients experienced a definite flare. See bar chart.

For patients with a baseline SLEDAI>2, treated patients had a 23.7% decrease in the risk of experiencing at least one definite flare, compared to placebo (p=0.201, log-rank test for time to first definite flare).

14.2 Reduction In Risk of Death

In the GL95-02 study (discussed above), five placebo patients died, and no prasterone-treated patients died. These data show a statistically significant and clinically meaningful reduction in risk of death by any cause. In the GL94-01, GL95-01 and GL95-02 clinical trials (pooled data), the prasterone treated group (including prasterone-treated crossover patients) experienced 8 deaths among 495 patients, or a risk of death of 1.62%. In contrast, the placebo group experienced 6 deaths among 77 patients, or a risk of death of 7.80%.

14.2.1 Clinical Study GL94-01

Study GL94-01 compared the proportion of patients achieving sustained reduction of daily corticosteroid dose, without worsening of signs and symptoms of SLE (“Responders”), in placebo (n = 64) and prasterone 200 mg (n = 64) groups for about 7 months.

For all randomized patients, 26/64 (41%) placebo and 35/64 (55%) prasterone 200 mg patients responded: a strong trend in favor of prasterone (p = 0.110). For patients with baseline SLEDAI >2, 13/45 (29%) placebo and 23/45 (51%) prasterone 200mg patients responded (p = 0.031).

15 HOW SUPPLIED / DOSAGE AND HANDLING

Prastera® softgels 200mg are oblong blue soft, liquid filled gelatin capsules.

Store at not more than 25° C (77° F). Excursions are permitted to 15° C to 30° C (59° F to 86° F). See United States Pharmacopoeia, Controlled Room Temperature. Protect from excessive moisture or humidity. Dispense in a tight, light-resistant container as defined in USP/NF, using a child-resistant closure system, accompanied by a Patient Insert and in a convenience pack together with a blister strip of ibuprofen 400mg oral tablets.

NDC 55607-400-10

Keep out of reach of children.

Manufactured for:
  Health Science Funding, LLC
  55 Madison Avenue, 4th floor
  Morristown, NJ 07960
  info@healthsciencefunding.com

16 PATIENT COUNSELING INFORMATION

See Medication Guide (§17) for specific patient instructions.

16.1 Patient / Caregiver Instructions

Inform patients of the following information before initiating therapy with PRASTERA® and periodically during the course of on-going therapy. Encourage patients to read the Medication Guide that accompanies each prescription dispensed, prior to using PRASTERA®.

16.2 Benefits

Oral prasterone 200 mg / day reduced the risk of auto-immune flare, §§6.2, 14.1, and significantly reduced the risk of death, §§6.4, 14.2, in placebo-controlled, randomized, blinded clinical studies (GL94-01, GL95-01, GL95-02 and GLB96-01) in female patients with Systemic Lupus Erythematosus. Results observed in clinical trials may not, however, reflect the rates observed in practice.

PRASTERA® does not cure, mitigate, treat or prevent the patient's underlying SLE. To the contrary, the patient will continue to have SLE. The patient therefore should continue to be monitored by a physician and should continue other therapy (e.g., prednisone, NSAID) as believed appropriate.

Oral prasterone reduced the risk of auto-immune flare and death. See above. PRASTERA® may not, however, make the patient feel significantly different on a day-to-day basis. This does not mean PRASTERA® is not working; it may take at least six months of continuous therapy to achieve a statistically-significant reduction in risk of flare and death. §14.

16.3 Other Medications

PRASTERA® is a synthetic form of 5-dehydroepiandrosterone. PRASTERA® should not be combined with dietary supplements containing “DHEA” or “dehydroepiandrosterone.”

PRASTERA® is a precursor to testosterone and estrogens. If PRASTERA® is used in conjunction with testosterone or estrogens, levels of serum testosterone and estrogens should be monitored closely to assure levels do not exceed the range seen in healthy women of similar age.

16.4 Adverse Reactions

PRASTERA® may cause acne. This acne is reversible on cessation of prasterone therapy, and may be treateable by a topical anti-acne drug. You may request a Prastera® convenience kit which includes a topical anti-acne drug.

PRASTERA® may cause hirsutism, reversible on cessation of prasterone therapy.

PRASTERA® may cause hypertension, §6.3.2, and/or changes in serum lipids, §7.2.4, or serum hormone levels, §7.2.1. These should be monitored, and are reversible on cessation of prasterone therapy.

16.5 Pregnancy

Instruct patients who are nursing, pregnant or intending to become pregnant, not to use PRASTERA®.

MEDICATION GUIDE

Prasterone is a naturally-occurring pre-hormone secreted by the adrenal cortex. SLE attacks the adrenal cortex. Women with SLE thus often have depressed levels of this pre-hormone.

Your doctor has prescribed PRASTERA® to supplement your body's level of this pre-hormone. Use PRASTERA® exactly as your doctor tells you.

You likely will not feel much different taking PRASTERA®. This does not mean that it is not working, so keep taking it unless your doctor tells you not to, or unless you feel you are having an adverse reaction to it.

In clinical studies, oral prasterone reduced lupus patients' risk of auto-immune flare and death. PRASTERA® does not, however, cure, mitigate, treat or prevent your SLE. Thus, even while taking your PRASTERA®, you will continue to have SLE. You therefore should continue to see your doctor and should continue other therapy they believe appropriate.

PRASTERA® may cause acne. If this happens, you can ask your doctor to give you a prescription for a PRASTERA® kit which includes a mild topical anti-acne treatment. If that does not work, talk with your health care provider because acne should go away simply by stopping PRASTERA®.

PRASTERA® may cause hirsutism (unwanted body hair). This is reversible by stopping taking PRASTERA®.

PRASTERA® may cause abdominal pain, hypertension, and/or changes in serum lipids or serum hormone levels; your doctor may want to monitor these.

Tell your doctor what other drugs or dietary supplements you are taking. If you are taking PRASTERA®, you should not use any dietary supplement containing “DHEA” or “dehydroepiandrosterone.”

If you are pregnant, intending to become pregnant, or are nursing, do not use PRASTERA®.

Store PRASTERA® at not more than 25° C (77° F), and protect from excessive moisture or humidity. Keep out of reach of children.

For medical advice about suspected side effects, call your doctor. You may report suspected side effects to your doctor, or the FDA at 1 (800) 332-1088, or to your pharmacist at 1 (855) FLARE-FREE.

Manufactured for:
  Health Science Funding, LLC
  55 Madison Avenue, 4th floor
  Morristown, NJ 07960
  info@healthsciencefunding.com

© 2012 Health Science Funding, LLC. All rights reserved. Patent pending. The PRASTERA name, PRASTERA device, product color scheme and package configuration are each trademarks of Health Science Funding, LLC.

IBUPROFEN - Ibuprofen Tablet

HEALTH SCIENCE FUNDING LLC

BOXED WARNING

Cardiovascular Risk

- NSAIDs may cause an increased risk of serious cardiovascular thrombotic events, myocardial infarction, and stroke, which can be fatal. This risk may increase with duration of use. Patients with cardiovascular disease or risk factors for cardiovascular disease may be at greater risk (see WARNINGS).
- Ibuprofen tablets are contraindicated for treatment of peri-operative pain in the setting of coronary artery bypass graft (CABG) surgery (see WARNINGS).

Gastrointestinal Risk

- NSAIDS cause an increased risk of serious gastrointestinal adverse events including bleeding, ulceration, and perforation of the stomach or intestines, which can be fatal. These events can occur at any time during use and without warning symptoms. Elderly patients are at greater risk for serious gastrointestinal events (see WARNINGS).

DESCRIPTION

Ibuprofen tablets contain the active ingredient ibuprofen, which is (±) - 2 - (p - isobutylphenyl) propionic acid. Ibuprofen is a white powder with a melting point of 74-77° C and is very slightly soluble in water (< 1 mg/mL) and readily soluble in organic solvents such as ethanol and acetone .
The structural formula is represented below:

Ibuprofen tablets, a nonsteroidal anti-inflammatory drug (NSAID), are available in 400 mg, 600 mg, and 800 mg tablets for oral administration. Inactive ingredients: colloidal silicon dioxide, croscarmellose sodium, magnesium stearate, microcrystalline cellulose, polyethylene glycol, polyvinyl alcohol, pregelatinized starch, talc and titanium dioxide.

CLINICAL PHARMACOLOGY

Ibuprofen tablets contain ibuprofen which possesses analgesic and antipyretic activities. Its mode of action, like that of other NSAIDs, is not completely understood, but may be related to prostaglandin synthetase inhibition.

In clinical studies in patients with rheumatoid arthritis and osteoarthritis , ibuprofen tablets have been shown to be comparable to aspirin in controlling pain and inflammation and to be associated with a statistically significant reduction in the milder gastrointestinal side effects (see ADVERSE REACTIONS). Ibuprofen tablets may be well tolerated in some patients who have had gastrointestinal side effects with aspirin, but these patients when treated with ibuprofen tablets should be carefully followed for signs and symptoms of gastrointestinal ulceration and bleeding. Although it is not definitely known whether ibuprofen tablets causes less peptic ulceration than aspirin, in one study involving 885 patients with rheumatoid arthritis treated for up to one year, there were no reports of gastric ulceration with ibuprofen tablets whereas frank ulceration was reported in 13 patients in the aspirin group (statistically significant p< .001).

Gastroscopic studies at varying doses show an increased tendency toward gastric irritation at higher doses. However, at comparable doses, gastric irritation is approximately half that seen with aspirin. Studies using 51Cr-tagged red cells indicate that fecal blood loss associated with ibuprofen tablets in doses up to 2400 mg daily did not exceed the normal range, and was significantly less than that seen in aspirin-treated patients.

In clinical studies in patients with rheumatoid arthritis, ibuprofen tablets have been shown to be comparable to indomethacin in controlling the signs and symptoms of disease activity and to be associated with a statistically significant reduction of the milder gastrointestinal (see ADVERSE REACTIONS) and CNS side effects.

Ibuprofen tablets may be used in combination with gold salts and/or corticosteroids.

Controlled studies have demonstrated that ibuprofen tablets are a more effective analgesic than propoxyphene for the relief of episiotomy pain, pain following dental extraction procedures, and for the relief of the symptoms of primary dysmenorrhea.

In patients with primary dysmenorrhea, ibuprofen tablets have been shown to reduce elevated levels of prostaglandin activity in the menstrual fluid and to reduce resting and active intrauterine pressure, as well as the frequency of uterine contractions. The probable mechanism of action is to inhibit prostaglandin synthesis rather than simply to provide analgesia .

The ibuprofen in ibuprofen tablets is rapidly absorbed. Peak serum ibuprofen levels are generally attained one to two hours after administration. With single doses up to 800 mg, a linear relationship exists between amount of drug administered and the integrated area under the serum drug concentration vs time curve. Above 800 mg, however, the area under the curve increases less than proportional to increases in dose. There is no evidence of drug accumulation or enzyme induction.

The administration of ibuprofen tablets either under fasting conditions or immediately before meals yields quite similar serum ibuprofen concentration-time profiles. When ibuprofen tablets are administered immediately after a meal, there is a reduction in the rate of absorption but no appreciable decrease in the extent of absorption. The bioavailability of the drug is minimally altered by the presence of food.

A bioavailability study has shown that there was no interference with the absorption of ibuprofen when ibuprofen tablets were given in conjunction with an antacid containing both aluminum hydroxide and magnesium hydroxide.

Ibuprofen is rapidly metabolized and eliminated in the urine . The excretion of ibuprofen is virtually complete 24 hours after the last dose. The serum half-life is 1.8 to 2.0 hours.

Studies have shown that following ingestion of the drug, 45%to 79%of the dose was recovered in the urine within 24 hours as metabolite A (25%), (+)-2-[p-(2hydroxymethyl-propyl) phenyl] propionic acid and metabolite B (37%), (+)-2-[p-(2carboxypropyl)phenyl] propionic acid; the percentages of free and conjugated ibuprofen were approximately 1%and 14%, respectively.

INDICATIONS AND USAGE

Carefully consider the potential benefits and risks of ibuprofen tablets and other treatment options before deciding to use ibuprofen tablets. Use the lowest effective dose for the shortest duration consistent with individual patient treatment goals (see WARNINGS).

Ibuprofen tablets are indicated for relief of the signs and symptoms of rheumatoid arthritis and osteoarthritis .

Ibuprofen tablets are indicated for relief of mild to moderate pain.

Ibuprofen tablets are also indicated for the treatment of primary dysmenorrhea.

Controlled clinical trials to establish the safety and effectiveness of ibuprofen tablets in children have not been conducted.

CONTRAINDICATIONS

Ibuprofen tablets are contraindicated in patients with known hypersensitivity to Ibuprofen.

Ibuprofen tablets should not be given to patients who have experienced asthma, urticaria , or allergic-type reactions after taking aspirin or other NSAIDs. Severe, rarely fatal, anaphylactic-like reactions to NSAIDs have been reported in such patients (see WARNINGS , Anaphylactoid Reactions, and PRECAUTIONS , Preexisting Asthma).

Ibuprofen tablets are contraindicated for the treatment of peri-operative pain in the setting of coronary artery bypass graft (CABG) surgery (see WARNINGS).

WARNINGS

Cardiovascular Effects

Cardiovascular Thrombotic Events

Clinical trials of several COX-2 selective and nonselective NSAIDs of up to three years duration have shown an increased risk of serious cardiovascular (CV) thrombotic events, myocardial infarction, and stroke , which can be fatal. All NSAIDs, both COX-2 selective and nonselective, may have a similar risk. Patients with known CV disease or risk factors for CV disease may be at greater risk. To minimize the potential risk for an adverse CV event in patients treated with an NSAID , the lowest effective dose should be used for the shortest duration possible. Physicians and patients should remain alert for the development of such events, even in the absence of previous CV symptoms. Patients should be informed about the signs and/or symptoms of serious CV events and the steps to take if they occur.

There is no consistent evidence that concurrent use of aspirin mitigates the increased risk of serious CV thrombotic events associated with NSAID use. The concurrent use of aspirin and an NSAID does increase the risk of serious GI events (see WARNINGS, Gastrointestinal Effects-Risk of Ulceration, Bleeding, and Perforation).

Two large, controlled clinical trials of a COX-2 selective NSAID for the treatment of pain in the first 10-14 days following CABG surgery found an increased incidence of myocardial infarction and stroke (see CONTRAINDICATIONS).

Hypertension

NSAIDs including ibuprofen tablets, can lead to onset of new hypertension or worsening of pre-existing hypertension, either of which may contribute to the increased incidence of CV events. Patients taking thiazides or loop diuretics may have impaired response to these therapies when taking NSAIDs. NSAIDs, including ibuprofen tablets, should be used with caution in patients with hypertension. Blood pressure (BP) should be monitored closely during the initiation of NSAID treatment and throughout the course of therapy.

Congestive Heart Failure and Edema

Fluid retention and edema have been observed in some patients taking NSAIDs. Ibuprofen tablets should be used with caution in patients with fluid retention or heart failure .

Gastrointestinal Effects-Risk of Ulceration, Bleeding, and Perforation

NSAIDs, including ibuprofen tablets, can cause serious gastrointestinal (GI) adverse events including inflammation, bleeding, ulceration, and perforation of the stomach, small intestine, or large intestine, which can be fatal. These serious adverse events can occur at any time, with or without warning symptoms, in patients treated with NSAIDs. Only one in five patients, who develop a serious upper GI adverse event on NSAID therapy, is symptomatic. Upper GI ulcers, gross bleeding, or perforation caused by NSAIDs occur in approximately 1%of patients treated for 3-6 months, and in about 2-4%of patients treated for one year. These trends continue with longer duration of use, increasing the likelihood of developing a serious GI event at some time during the course of therapy. However, even short-term therapy is not without risk. NSAIDs should be prescribed with extreme caution in those with a prior history of ulcer disease or gastrointestinal bleeding. Patients with a prior history of peptic ulcer disease and/or gastrointestinal bleeding who use NSAIDs have a greater than 10-fold increased risk for developing a GI bleed compared to patients treated with neither of these risk factors. Other factors that increase the risk of GI bleeding in patients treated with NSAIDs include concomitant use of oral corticosteroids or anticoagulants, longer duration of NSAID therapy, smoking, use of alcohol, older age, and poor general health status. Most spontaneous reports of fatal GI events are in elderly or debilitated patients and therefore, special care should be taken in treating this population.

To minimize the potential risk for an adverse GI event in patients treated with an NSAID, the lowest effective dose should be used for the shortest possible duration. Patients and physicians should remain alert for signs and symptoms of GI ulcerations and bleeding during NSAID therapy and promptly initiate additional evaluation and treatment if a serious GI event is suspected. This should include discontinuation of the NSAID until a serious GI adverse event is ruled out. For high-risk patients, alternate therapies that do not involve NSAIDs should be considered.

Renal Effects

Long-term administration of NSAIDs has resulted in renal papillary necrosis and other renal injury. Renal toxicity has also been seen in patients in whom renal prostaglandins have a compensatory role in the maintenance of renal perfusion. In these patients, administration of a NSAID may cause a dose-dependent reduction in prostaglandin formation and, secondarily, in renal blood flow, which may precipitate overt renal decompensation. Patients at greatest risk of this reaction are those with impaired renal function, heart failure, liver dysfunction, those taking diuretics and ACE inhibitors, and the elderly. Discontinuation of NSAID therapy is usually followed by recovery to the pretreatment state.

Advanced Renal Disease

No information is available from controlled clinical studies regarding the use of ibuprofen tablets in patients with advanced renal disease. Therefore, treatment with ibuprofen tablets is not recommended in these patients with advanced renal disease. If ibuprofen tablet therapy must be initiated, close monitoring of the patients renal function is advisable.

Anaphylactoid Reactions

As with other NSAIDs, anaphylactoid reactions may occur in patients without known prior exposure to ibuprofen tablets. Ibuprofen tablets should not be given to patients with the aspirin triad. This symptom complex typically occurs in asthmatic patients who experience rhinitis with or without nasal polyps, or who exhibit severe, potentially fatal bronchospasm after taking aspirin or other NSAIDs (see CONTRAINDICATIONSand PRECAUTIONS, Preexisting Asthma). Emergency help should be sought in cases where an anaphylactoid reaction occurs.

Skin Reactions

NSAIDs, including ibuprofen tablets, can cause serious skin adverse events such as exfoliative dermatitis , Stevens-Johnson Syndrome (SJS), and toxic epidermal necrolysis (TEN), which can be fatal. These serious events may occur without warning. Patients should be informed about the signs and symptoms of serious skin manifestations and use of the drug should be discontinued at the first appearance of skin rash or any other sign of hypersensitivity.

Pregnancy

In late pregnancy, as with other NSAIDs, ibuprofen tablets should be avoided because it may cause premature closure of the ductus arteriosus.

PRECAUTIONS

General Precautions

Ibuprofen tablets cannot be expected to substitute for corticosteroids or to treat corticosteroid insufficiency. Abrupt discontinuation of corticosteroids may lead to disease exacerbation. Patients on prolonged corticosteroid therapy should have their therapy tapered slowly if a decision is made to discontinue corticosteroids.

The pharmacological activity of ibuprofen tablets in reducing fever and inflammation may diminish the utility of these diagnostic signs in detecting complications of presumed noninfectious, painful conditions.

Information for Patients

Patients should be informed of the following information before initiating therapy with an NSAID and periodically during the course of ongoing therapy. Patients should also be encouraged to read the NSAID Medication Guide that accompanies each prescription dispensed.

- Ibuprofen tablets like other NSAIDs, may cause serious CV side effects, such as MI or stroke, which may result in hospitalization and even death. Although serious CV events can occur without warning symptoms, patients should be alert for the signs and symptoms of chest pain , shortness of breath, weakness, slurring of speech, and should ask for medical advice when observing any indicative sign or symptoms. Patients should be apprised of the importance of this follow-up (see WARNINGS, Cardiovascular Effects).
- Ibuprofen tablets, like other NSAIDs, can cause GI discomfort and, rarely, serious GI side effects, such as ulcers and bleeding, which may result in hospitalization and even death. Although serious GI tract ulcerations and bleeding can occur without warning symptoms, patients should be alert for the signs and symptoms of ulcerations and bleeding, and should ask for medical advice when observing any indicative signs or symptoms including epigastric pain, dyspepsia , melena , and hematemesis . Patients should be apprised of the importance of this follow-up (see WARNINGS, Gastrointestinal Effects- Risk of Ulceration, Bleeding and Perforation).
- Ibuprofen tablets, like other NSAIDs, can cause serious skin side effects such as exfoliative dermatitis, SJS and TEN, which may result in hospitalization and even death. Although serious skin reactions may occur without warning, patients should be alert for the signs and symptoms of skin rash and blisters, fever, or other signs hypersensitivity such as itching, and should ask for medical advice when observing any indicative sign or symptoms. Patients should be advised to stop the drug immediately if they develop any type of rash and contact their physicians as soon as possible.
- Patients should promptly report signs or symptoms of unexplained weight gain or edema to their physicians.
- Patients should be informed of the warning signs and symptoms of hepatotoxicity (e.g., nausea, fatigue, lethargy, pruritus, jaundice, right upper quadrant tenderness and "flu-like" symptoms). If these occur, patients should be instructed to stop therapy and seek immediate medical therapy.
- Patients should be informed of the signs of an anaphylactoid reaction (e.g. difficulty breathing, swelling of the face or throat). If these occur, patients should be instructed to seek immediate emergency help (see WARNINGS).
- In late pregnancy, as with other NSAIDs, ibuprofen tablets should be avoided because it may cause premature closure of the ductus arteriosus.

Laboratory Tests

Because serious GI tract ulcerations and bleeding can occur without warning symptoms, physicians should monitor for signs or symptoms of GI bleeding. Patients on long-term treatment with NSAIDs should have their CBC and chemistry profile checked periodically. If clinical signs and symptoms consistent with liver or renal disease develop, systemic manifestations occur (e.g., eosinophilia, rash etc.), or abnormal liver tests persist or worsen, ibuprofen tablets should be discontinued.

Drug Interactions

ACE-inhibitors

Reports suggest that NSAIDs may diminish the antihypertensive effect of ACE-inhibitors. This interaction should be given consideration in patients taking NSAIDs concomitantly with ACE-inhibitors.

Aspirin

When ibuprofen tablets are administered with aspirin, its protein binding is reduced, although the clearance of free ibuprofen tablets is not altered. The clinical significance of this interaction is not known; however, as with other NSAIDs, concomitant administration of ibuprofen and aspirin is not generally recommended because of the potential for increased adverse effects.

Diuretics

Clinical studies, as well as post marketing observations, have shown that ibuprofen tablets can reduce the natriuretic effect-of furosemide and thiazides in some patients. This response has been attributed to inhibition of renal prostaglandin synthesis. During concomitant therapy with NSAIDs, the patient should be observed closely for signs of renal failure (see WARNINGS , Renal Effects), as well as to assure diuretic efficacy.

Lithium

Ibuprofen produced an elevation of plasma lithium levels and a reduction in renal lithium clearance in a study of eleven normal volunteers. The mean minimum lithium concentration increased 15%and the renal clearance of lithium was decreased by 19%during this period of concomitant drug administration. This effect has been attributed to inhibition of renal prostaglandin synthesis by ibuprofen. Thus, when ibuprofen and lithium are administered concurrently, subjects should be observed carefully for signs of lithium toxicity. (Read circulars for lithium preparation before use of such concurrent therapy.)

Methotrexate

NSAIDs have been reported to competitively inhibit methotrexate accumulation in rabbit kidney slices. This may indicate that they could enhance the toxicity of methotrexate. Caution should be used when NSAIDs are administered concomitantly with methotrexate.

Warfarin-type anticoagulants

Several short-term controlled studies failed to show that ibuprofen tablets significantly affected prothrombin times or a variety of other clotting factors when administered to individuals on coumarin-type anticoagulants. However, because bleeding has been reported when ibuprofen tablets and other NSAIDs have been administered to patients on coumarin-type anticoagulants, the physician should be cautious when administering ibuprofen tablets to patients on anticoagulants. The effects of warfarin and NSAIDs on GI bleeding are synergistic, such that the users of both drugs together have a risk of serious GI bleeding higher than users of either drug alone.

H-2 Antagonists

In studies with human volunteers, co-administration of cimetidine or ranitidine with ibuprofen had no substantive effect on ibuprofen serum concentrations.

Pregnancy

Teratogenic Effects

Reproductive studies conducted in rats and rabbits have not demonstrated evidence of developmental abnormalities. However, animal reproduction studies are not always predictive of human response. There are no adequate and well-controlled studies in pregnant women. Ibuprofen tablets should be used in pregnancy only if the potential benefit justifies the potential risk to the fetus .

Nonteratogenic Effects

Because of the known effects of NSAIDs on the fetal cardiovascular system (closure of ductus arteriosus), use during late pregnancy should be avoided.

Labor And Delivery

In rat studies with NSAIDs, as with other drugs known to inhibit prostaglandin synthesis, an increased incidence of dystocia , delayed parturition , and decreased pup survival occurred. The effects of ibuprofen tablets on labor and delivery in pregnant women are unknown.

Nursing Mothers

It is not known whether this drug is excreted in human milk. Because many drugs are excreted in human-milk and because of the potential for serious adverse reactions in nursing infants from ibuprofen tablets, a decision should be made whether to discontinue nursing or discontinue the drug, taking into account the importance of the drug to the mother.

Pediatric Use

Safety and effectiveness of ibuprofen tablets in pediatric patients have not been established.

Geriatric Use

As with any NSAIDs, caution should be exercised in treating the elderly (65 years and older).

Hepatic effects

Borderline elevations of one or more liver tests may occur in up to 15%of patients taking NSAIDs, including ibuprofen tablets. These laboratory abnormalities may progress, may remain unchanged, or may be transient with continuing therapy. Notable elevations of ALT or AST (approximately three or more times the upper limit of normal) have been reported in approximately 1%of patients in clinical trials with NSAIDs. In addition, rare cases of severe hepatic reactions, including jaundice , fulminant hepatitis , liver necrosis, and hepatic failure, some of them with fatal outcomes have been reported.

A patient with symptoms and/or signs suggesting liver dysfunction, or with abnormal liver test values, should be evaluated for evidence of the development of a more severe hepatic reaction while on therapy with ibuprofen tablets. If clinical signs and symptoms consistent with liver disease develop, or if systemic manifestations occur (e.g., eosinophilia , rash, etc.), ibuprofen tablets should be discontinued.

Hematological effects

Anemia is sometimes seen in patients receiving NSAIDs, including ibuprofen tablets. This may be due to fluid retention, occult or gross GI blood loss, or an incompletely described effect upon erythropoiesis. Patients on long-term treatment with NSAIDs, including ibuprofen tablets, should have their hemoglobin or hematocrit checked if they exhibit any signs or symptoms of anemia.

In two postmarketing clinical studies the incidence of a decreased hemoglobin level was greater than previously reported. Decrease in hemoglobin of 1 gram or more was observed in 17.1%of 193 patients on 1600 mg ibuprofen daily (osteoarthritis), and in 22.8%of 189 patients taking 2400 mg of ibuprofen daily (rheumatoid arthritis). Positive stool occult blood tests and elevated serum creatinine levels were also observed in these studies.

NSAIDs inhibit platelet aggregation and have been shown to prolong bleeding time in some patients. Unlike aspirin, their effect on platelet function is quantitatively less, of shorter duration, and reversible.

Patients receiving ibuprofen tablets who may be adversely affected by alterations in platelet function, such as those with coagulation disorders or patients receiving anticoagulants should be carefully monitored.

Preexisting asthma

Patients with asthma may have aspirin-sensitive asthma. The use of aspirin in patients with aspirin-sensitive asthma has been associated with severe bronchospasm, which can be fatal. Since cross reactivity, including bronchospasm, between aspirin and NSAIDs has been reported in such aspirin-sensitive patients, ibuprofen tablets should not be administered to patients with this form of aspirin sensitivity and should be used with caution in patients with preexisting asthma.

Ophthalmological effects

Blurred and/or diminished vision, scotomata, and/or changes in color vision have been reported. If a patient develops such complaints while receiving ibuprofen tablets, the drug should be discontinued, and the patient should have an ophthalmologic examination which includes central visual fields and color vision testing.

Aseptic meningitis

Aseptic meningitis with fever and coma has been observed on rare occasions in patients on ibuprofen therapy. Although it is probably more likely to occur in patients with systemic lupus erythematosus and related connective tissue diseases, it has been reported in patients who do not have an underlying chronic disease . If signs or symptoms of meningitis develop in a patient on ibuprofen tablets, the possibility of its being related to ibuprofen tablets should be considered.

ADVERSE REACTIONS

The most frequent type of adverse reaction occurring with ibuprofen tablets is gastrointestinal . In controlled clinical trials the percentage of patients reporting one or more gastrointestinal complaints ranged from 4%to 16%.

In controlled studies when ibuprofen tablets were compared to aspirin and indomethacin in equally effective doses, the overall incidence of gastrointestinal complaints was about half that seen in either the aspirin- or indomethacin-treated patients.

Adverse reactions observed during controlled clinical trials at an incidence greater than 1%are listed in the table. Those reactions listed in Column one encompass observations in approximately 3,000 patients. More than 500 of these patients were treated for periods of at least 54 weeks.

Still other reactions occurring less frequently than 1 in 100 were reported in controlled clinical trials and from marketing experience. These reactions have been divided into two categories: Column two of the table lists reactions with therapy with ibuprofen tablets where the probability of a causal relationship exists: for the reactions in Column three, a causal relationship with ibuprofen tablets has not been established.

Reported side effects were higher at doses of 3200 mg/day than at doses of 2400 mg or less per day in clinical trials of patients with rheumatoid arthritis . The increases in incidence were slight and still within the ranges reported in the table.

Incidence Greater than 1% (but less than 3%) probable casual Relationship | Precise Incidence Unknown (but less than 1%) probable Casual Relationship* | Precise Incidence Unknown (but less than 1%) Casual Relationship Unknown*
GASTROINTESTINAL Nausea†, epigastric paint†, heartburn, diarrhea, abdominal distress, nausea and vomiting, indigestion, constipation, abdominal cramps or Pain, fullness of GI tract (bloating and flatulence) | Gastric or duodenal ulcer with bleeding and/or perforation, gastrointestinal hemorrhage, melena, gastritis, hepatitis, jaundice, abnormal liver function tests; pancreatis
CENTRAL NERVOUS SYSTEM Dizziness†, headache, nervousness | Depression, insomnia, confusion, emotional liability, somnolence, aseptic meningitis with fever and coma (see PRECAUTIONS) | Paresthesias, hallucinations, dream abnormalities, pseudo-tumor cerebri
DERMATOLOGIC Rash† (including maculopapular type), pruritis | Vesiculobullous eruptions, urticaria, erythema multiforme, Stevens-Johnson syndrome, alopecia | Toxic epidermal necrolysis, photoallergic skin reactions
SPECIAL SENSES Tinnitus | Hearing loss, amblyopia (blurred and/or diminished vision, scotomata and/or changes in color vision) (see PRECAUTIONS) | Conjuctivitis, diplopia, optic neuritis, cataracts
HEMATOLOGIC | Neutropenia, agranulocytosis, aplastic anemia, hemolytic anemia (sometimes Coombs positive), thrombocytopenia with or without purpura, eosinophilia, decreases in hemoglobin and hematocrit (see PRECAUTIONS) | Bleeding episodes (eg epistaxis, menorrhagia)
METABOLIC/ENDOCRINE Decreased appetite |  | Gynecomastia, hypoglycemic reaction, acidosis
CARDIOVASCULAR Edema, fluid retention (generally responds promptly to drug discontinuation) (see PRECAUTIONS) | Congestive heart failure in patients with marginal cardiac function elevated blood pressure, palpitations | Arrhythmias (sinus tachycardia, sinus bradycardia)
ALLERGIC | Syndrome of abdominal pain, fever, chills, nausea and vomiting; anaphylaxis; bronchospasm (see CONTRADICATIONS) | Serum sickness, lupuserythematosus syndrome, Henoch-Schonlein vasculitis, angioedema
RENAL | Acute renal failure see PRECAUTIONS), decreased creatinine clearance, polyuria, azotemia, cystitis, Hematuria | Renal papillary necrosis
MISCELLANEOUS | Dry eyes and mouth, gingival ulcer, rhinitis
* Reactions are classified under "Probable Causal Relationship (PCR)" if there has been one positive rechallenge or if three or more cases occur which might be causally related. Reactions are classified under "Causal Relationship Unknown" if seven or more events have been reported but the criteria for PCR have not been met.
† Reactions occurring in 3% to 9% of patients treated with ibuprofen tablets. (Those reactions occurring in less than 3% of the patients are unmarked).

OVERDOSAGE

Approximately 1½ hours after the reported ingestion of from 7 to 10 ibuprofen tablets (400 mg), a 19-month old child weighing 12 kg was seen in the hospital emergency room, apneic and cyanotic , responding only to painful stimuli. This type of stimulus, however, was sufficient to induce respiration . Oxygen and parenteral fluids were given; a greenish-yellow fluid was aspirated from the stomach with no evidence to indicate the presence of ibuprofen . Two hours after ingestion the child's condition seemed stable; she still responded only to painful stimuli and continued to have periods of apnea lasting from 5 to 10 seconds. She was admitted to intensive care and sodium bicarbonate was administered as well as infusions of dextrose and normal saline. By four hours post-ingestion she could be aroused easily, sit by herself and respond to spoken commands. Blood level of ibuprofen was 102.9 μg/mL approximately 8½ hours after accidental ingestion. At 12 hours she appeared to be completely recovered.

In two other reported cases where children (each weighing approximately 10 kg) accidentally, acutely ingested approximately 120 mg/kg, there were no signs of acute intoxication or late sequelae . Blood level in one child 90 minutes after ingestion was 700 μg/mL — about 10 times the peak levels seen in absorption-excretion studies.

A 19-year old male who had taken 8,000 mg of ibuprofen over a period of a few hours complained of dizziness , and nystagmus was noted. After hospitalization, parenteral hydration and three days bed rest, he recovered with no reported sequelae.

In cases of acute overdosage, the stomach should be emptied by vomiting or lavage, though little drug will likely be recovered if more than an hour has elapsed since ingestion. Because the drug is acidic and is excreted in the urine, it is theoretically beneficial to administer alkali and induce diuresis . In addition to supportive measures, the use of oral activated charcoal may help to reduce the absorption and reabsorption of ibuprofen tablets.

DOSAGE AND ADMINISTRATION

Carefully consider the potential benefits and risks of ibuprofen tablets and other treatment options before deciding to use ibuprofen tablets. Use the lowest effective dose for the shortest duration consistent with individual patient treatment goals (see WARNINGS).

After observing the response to initial therapy with ibuprofen tablets, the dose and frequency should be adjusted to suit an individual patient's needs.

Do not exceed 3200 mg total daily dose. If gastrointestinal complaints occur, administer ibuprofen tablets with meals or milk.

Rheumatoid arthritis and osteoarthritis, including flare-ups of chronic disease

Suggested Dosage: 1200 mg-3200 mg daily (300 mg qid; 400 mg, 600 mg or 800 mg tid or qid). Individual patients may show a better response to 3200 mg daily, as compared with 2400 mg, although in well-controlled clinical trials patients on 3200 mg did not show a better mean response in terms of efficacy. Therefore, when treating patients with 3200 mg/day, the physician should observe sufficient increased clinical benefits to offset potential increased risk.

The dose should be tailored to each patient, and may be lowered or raised depending on the severity of symptoms either at time of initiating drug therapy or as the patient responds or fails to respond.

In general, patients with rheumatoid arthritis seem to require higher doses of ibuprofen tablets than do patients with osteoarthritis.

The smallest dose of ibuprofen tablets that yields acceptable control should be employed. A linear blood level dose-response relationship exists with single doses up to 800 mg (See CLINICAL PHARMACOLOGY for effects of food on rate of absorption).

The availability of four tablet strengths facilitates dosage adjustment.

In chronic conditions , a therapeutic response to therapy with ibuprofen tablets is sometimes seen in a few days to a week but most often is observed by two weeks. After a satisfactory response has been achieved, the patient's dose should be reviewed and adjusted as required.

Mild to moderate pain: 400 mg every 4 to 6 hours as necessary for relief of pain.

In controlled analgesic clinical trials, doses of ibuprofen tablets greater than 400 mg were no more effective than the 400 mg dose.

Dysmenorrhea

For the treatment of dysmenorrhea, beginning with the earliest onset of such pain, ibuprofen tablets should be given in a dose of 400 mg every 4 hours as necessary for the relief of pain.

HOW SUPPLIED

Ibuprofen tablets are available in the following strengths:

400 mg (white to off white, round, biconvex, film coated tablets debossed with ‘121' on one side and plain on other side)

Blister strips of 5 (NDC 55607-400-10)

Store at controlled room temperature 20° to 25°C (68° to 77°F) [see USP].

Rx only

Manufactured for:
Health Science Funding, LLC
Morristown, NJ 07960 USA

Manufactured by:
Marksans Pharma Ltd.
Verna, Goa-403 722, India

Iss. 03/14

SPL Medguide

Medication Guide for Non-Steroidal Anti-Inflammatory Drugs (NSAIDs)

(See the end of this Medication Guide for a list of prescription NSAID medicines)

What is the most important information I should know about medicines called Non-Steroidal Anti-Inflammatory Drugs (NSAIDs)?

NSAID medicines may increase the chance of a heart attack or stroke that can lead to death. This chance increases:

- with longer use of NSAID medicines
- in people who have heart disease

NSAID medicines should never be used right before or after a heart surgery called a "coronary artery bypass graft (CABG)."

NSAID medicines can cause ulcers and bleeding in the stomach and intestines at any time during treatment. Ulcers and bleeding:

- can happen without warning symptoms
- may cause death

The chance of a person getting an ulcer or bleeding increases with:

- taking medicines called "corticosteroids" and "anticoagulants"
- longer use
- smoking
- drinking alcohol
- older age
- having poor health

NSAID medicines should only be used:

- exactly as prescribed
- at the lowest dose possible for your treatment
- for the shortest time needed

What are Non-Steroidal Anti-Inflammatory Drugs (NSAIDs)?

NSAID medicines are used to treat pain and redness, swelling, and heat (inflammation) from medical conditions such as:

- different types of arthritis
- menstrual cramps and other types of short-term pain

Who should not take a Non-Steroidal Anti-Inflammatory Drug (NSAID)?

Do not take an NSAID medicine:

- if you had an asthma attack, hives, or other allergic reaction with aspirin or any other NSAID medicine
- for pain right before or after heart bypass surgery

Tell your healthcare provider:

- about all of your medical conditions
- about all of the medicines you take. NSAIDs and some other medicines can interact with each other and cause serious side effects. Keep a list of your medicines to show to your healthcare provider and pharmacist.
- if you are pregnant. NSAID medicines should not be used by pregnant women late in their pregnancy.
- if you are breastfeeding. Talk to your doctor.

What are the possible side effects of Non-Steroidal Anti-Inflammatory Drugs (NSAIDs)?

Serious side effects include:

- heart attack
- stroke
- high blood pressure
- heart failure from body swelling (fluid retention)
- kidney problems including kidney failure
- bleeding and ulcers in the stomach and intestine
- low red blood cells (anemia)
- life-threatening skin reactions
- life-threatening allergic reactions
- liver problems including liver failure
- asthma attacks in people who have asthma

Other side effects include:

- stomach pain
- constipation
- diarrhea
- gas
- heartburn
- nausea
- vomiting
- dizziness

Get emergency help right away if you have any of the following symptoms:

- shortness of breath or trouble breathing
- chest pain
- weakness in one part or side of your body
- slurred speech
- swelling of the face or throat

Stop your NSAID medicine and call your healthcare provider right away if you have any of the following symptoms:

- nausea
- more tired or weaker than usual
- itching
- your skin or eyes look yellow
- stomach pain
- flu-like symptoms
- vomit blood
- there is blood in your bowel movement or it is black and sticky like tar
- unusual weight gain
- skin rash or blisters with fever
- swelling of the arms and legs, hands and feet

These are not all the side effects with NSAID medicines. Talk to your healthcare provider or pharmacist for more information about NSAID medicines.

Other information about Non-Steroidal Anti-Inflammatory Drugs (NSAIDs)

- Aspirin is an NSAID medicine but it does not increase the chance of a heart attack. Aspirin can cause bleeding in the brain, stomach, and intestines. Aspirin can also cause ulcers in the stomach and intestines.
- Some of these NSAID medicines are sold in lower doses without a prescription (over-the-counter). Talk to your healthcare provider before using over-the-counter NSAIDs for more than 10 days.

NSAID medicines that need a prescription

Generic Name | Tradename
Celecoxib | Celebrex
Diclofenac | Cataflam, Volataren, Arthrotec (combined with misoprostol)
Diflunisal | Dolobid
Etodolac | Lodine, Lodine XL
Fenoprofen | Nalfon, Nalfon 200
Flurbiprofen | Ansaid
Ibuprofen | Motrin, Tab-Profen, Vicoprofen* (combined with hydrocodone), combunox (combined with oxycodone)
Indomethacin | Indocin, Indocin SR, Indo-Lemmon, Indomethagan
Ketoprofen | Oruvail
Ketorolac | Toradol
Mefenamic Acid | Ponstel
Meloxicam | Mobic
Nabumetone | Relafen
Naproxen | Naprosyn, Anaprox, Anaprox DS, EC-Naproxyn, Naprelan, Naprapac (copackaged with lansoprazole)
Oxaprozin | Daypro
Piroxicam | Feldene
Sulindac | Clinoril
Tolmetin | Tolectin, Tolectin DS, Tolectin 600

*Vicoprofen contains the same dose of ibuprofen as over-the-counter (OTC) NSAIDs, and is usually used for less than 10 days to treat pain. The OTC NSAID label warns that long term continuous use may increase the risk of heart attack or stroke.

This Medication Guide has been approved by the U.S. Food and Drug Administration.

Manufactured for:
Health Science Funding, LLC
Morristown, NJ 07960 USA

Manufactured by:
Marksans Pharma Ltd.
Verna, Goa-403 722, India

Iss. 03/14

Principal Display Panel - Capsule Label

Prasterone 200mg

Contents: 15 softgels.

Directions: One softgel daily.

Principal Display Panel - Blister Label

NDC 55607-400-10

Rx Only

Prastera®

Ibuprofen
Tablets USP

400 mg

5 tablets

Health Science
Funding LLC

Principal Display Panel - Kit Label

Prastera® Kit

Rx only.

Keep away from children.

See package inserts for
complete prescribing
and use information

NDC 55607-400-10

Kit includes:

- Blue prasterone softgels
- White ibuprofen solid tablets